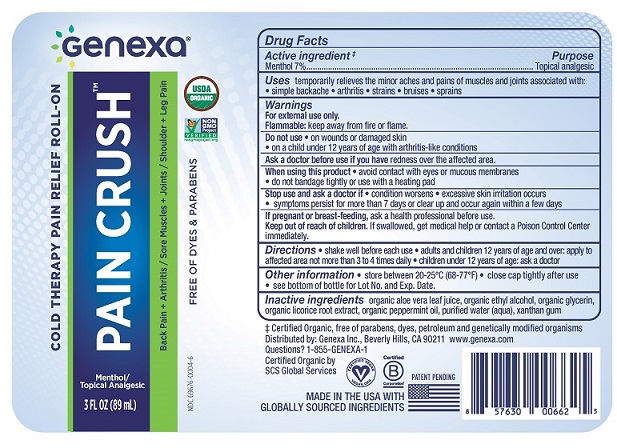 DRUG LABEL: Pain Crush
NDC: 69676-0004 | Form: GEL
Manufacturer: Genexa Inc.
Category: otc | Type: HUMAN OTC DRUG LABEL
Date: 20190814

ACTIVE INGREDIENTS: MENTHOL 7 g/100 mL
INACTIVE INGREDIENTS: ALOE VERA LEAF; WATER; GLYCERIN; XANTHAN GUM; ALCOHOL; LICORICE; PEPPERMINT OIL

Pain Crush

Drug Facts

Active ingredient^+

Menthol 7%

Purpose

Topical analgesic

INDICATIONS AND USAGE

Uses temporarily relieves the minor aches and pains of muscles and joints associated with:

- simple backache
- arthritis
- strains
- bruises
- sprains

Warnings

For external use only.

Flammable. Keep away from fire or flame.

Do not use

- on wounds or damaged skin
- on a child under 12 years of age with arthritis-like conditions

Ask a doctor before use if you have redness over the affected area.

When using this product

- avoid contact with eyes or mucous membranes
- do not bandage tightly or use with a heating pad

Stop use and ask a doctor if

- condition worsens
- symptoms persist for more than 7 days or clear up and occur again within a few days
- excessive skin irritation occurs

PREGNANCY OR BREAST FEEDING

If pregnant or breast-feeding, ask a doctor before use.

Keep out of reach of children. If swallowed, get medical help or contact a Poison Control Center immediately.

Directions

- shake well before each use
- adults and children 12 years of age and over: apply to affected area not more than 3 to 4 times daily
- children under 12 years of age: ask a doctor

Other information

- store between 20 to 25°C (68 to 77°F)
- close cap tightly after use
- see bottom of bottle for Lot No. and Exp. Date.

Inactive ingredients

organic aloe vera leaf juice, organic ethyl alcohol, organic glycerin, organic licorice root extract, organic peppermint oil, purified water (aqua), xanthan gum

+Certified Organic, free of parabens, dyes, petroleum and genetically modified organisms

Distributed by: Genexa Inc., Beverly Hills, CA 90211 www.genexa.com

Questions? 1-855-GENEXA-1

Certified Organic by SCS Global Services

MADE IN THE USA WITH GLOBALLY SOURCED INGREDIENTS

PACKAGE LABEL

Genexa®

COLD THERAPY PAIN RELIEF ROLL ON

PAIN CRUSH™

Menthol / Topical Analgesic

3 FL OZ (89 mL)

Back Pain + Arthritis / Sore Muscles + Joints / Shoulder + Leg Pain

USDA ORGANIC

NON GMO Project VERIFIED

FREE OF DYES & PARABENS

NDC 69676-0004-6